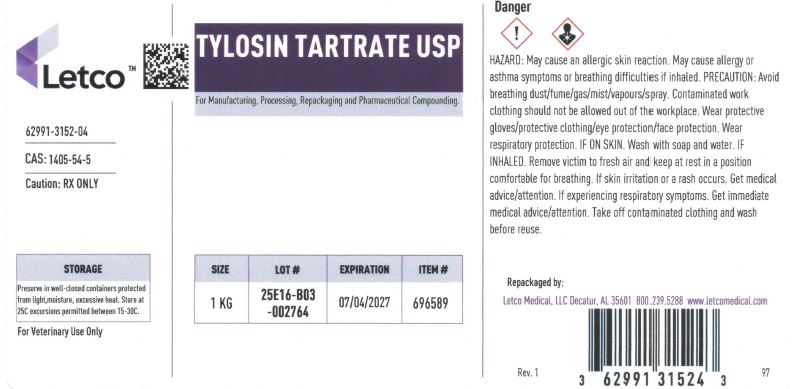 DRUG LABEL: TYLOSIN TARTRATE
NDC: 62991-3152 | Form: POWDER
Manufacturer: LETCO MEDICAL, LLC
Category: other | Type: BULK INGREDIENT - ANIMAL DRUG
Date: 20250627

ACTIVE INGREDIENTS: TYLOSIN TARTRATE 1 g/1 g

Tylosin Tartrate USP

PACKAGE LABEL

Tylosin Tartrate USP 1kg